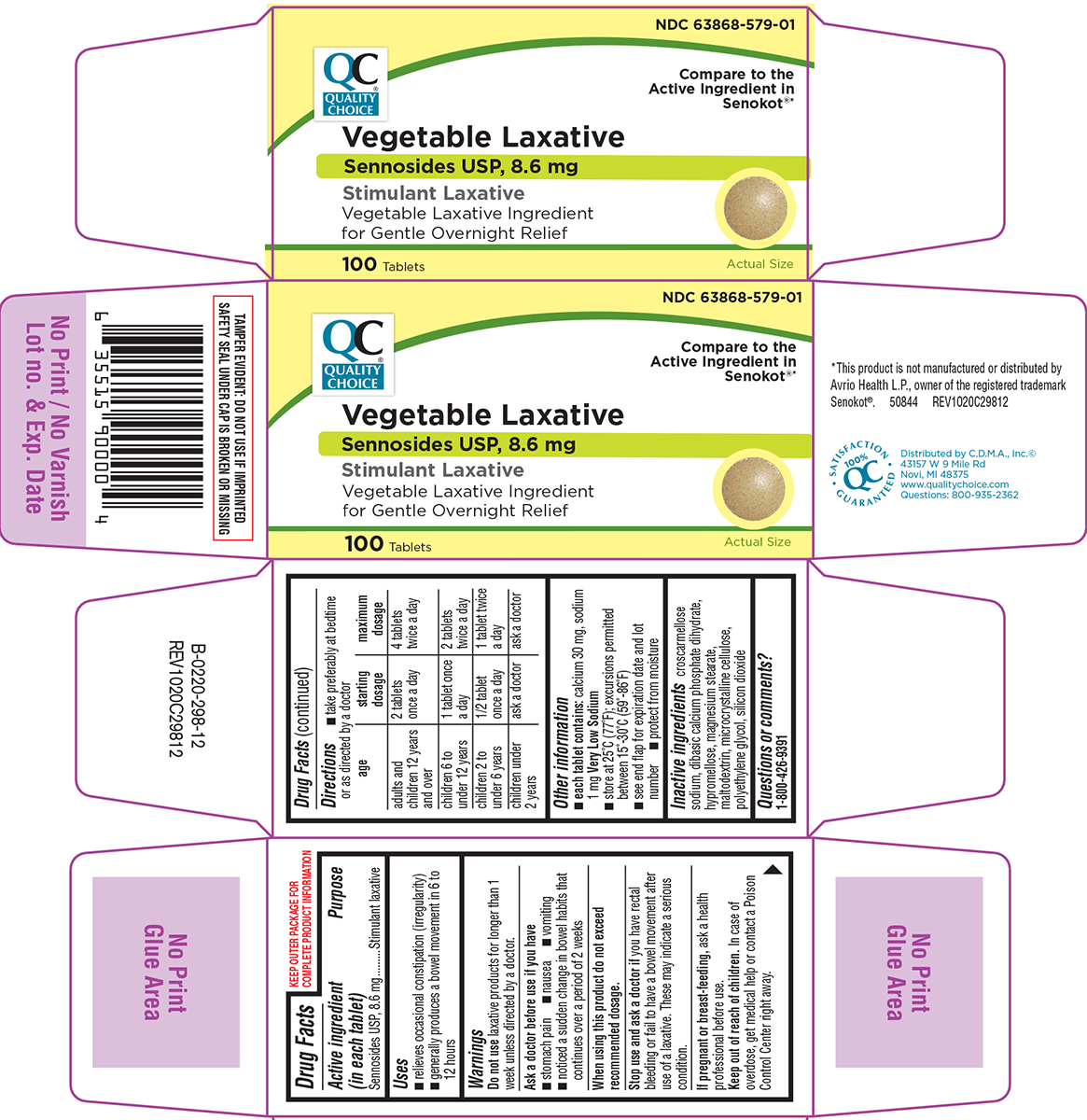 DRUG LABEL: Vegetable Laxative
NDC: 63868-579 | Form: TABLET, FILM COATED
Manufacturer: CHAIN DRUG MARKETING ASSOCIATION INC
Category: otc | Type: HUMAN OTC DRUG LABEL
Date: 20251215

ACTIVE INGREDIENTS: SENNOSIDES 8.6 mg/1 1
INACTIVE INGREDIENTS: CROSCARMELLOSE SODIUM; DIBASIC CALCIUM PHOSPHATE DIHYDRATE; HYPROMELLOSE, UNSPECIFIED; MAGNESIUM STEARATE; MALTODEXTRIN; MICROCRYSTALLINE CELLULOSE; POLYETHYLENE GLYCOL, UNSPECIFIED; SILICON DIOXIDE

Quality Choice 44-298

Active ingredient (in each tablet)

Sennosides USP, 8.6 mg

Purpose

Stimulant laxative

Uses

- relieves occasional constipation (irregularity)
- generally produces a bowel movement in 6 to 12 hours

Warnings

Do not use

laxative products for longer than 1 week unless directed by a doctor.

Ask a doctor before use if you have

- stomach pain
- nausea
- vomiting
- noticed a sudden change in bowel habits that continues over a period of 2 weeks

When using this product

do not exceed recommended dosage.

Stop use and ask a doctor if

you have rectal bleeding or fail to have a bowel movement after use of a laxative. These may indicate a serious condition.

If pregnant or breast-feeding,

ask a health professional before use.

Keep out of reach of children.

In case of overdose, get medical help or contact a Poison Control Center right away.

Directions

- take preferably at bedtime or as directed by a doctor

age | starting dosage | maximum dosage
adults and children 12 years and over | 2 tablets once a day | 4 tablets twice a day
children 6 to under 12 years | 1 tablet once a day | 2 tablets twice a day
children 2 to under 6 years | 1/2 tablet once a day | 1 tablet twice a day
children under 2 years | ask a doctor | ask a doctor

Other information

- each tablet contains: calcium 30 mg, sodium 1 mg Very Low Sodium
- store at 25ºC (77ºF); excursions permitted between 15º-30ºC (59º-86ºF)
- protect from moisture
- see end flap for expiration date and lot number

Inactive ingredients

croscarmellose sodium, dibasic calcium phosphate dihydrate, hypromellose, magnesium stearate, maltodextrin, microcrystalline cellulose, polyethylene glycol, silicon dioxide

Questions or comments?

1-800-426-9391

Principal display panel

QC®
QUALITY
CHOICE

NDC 63868-579-01

Compare to the
Active Ingredient in
Senokot®*

Vegetable Laxative
Sennosides USP, 8.6 mg

Stimulant Laxative
Vegetable Laxative Ingredient
for Gentle Overnight Relief

100 Tablets

Actual Size

TAMPER EVIDENT: DO NOT USE IF IMPRINTED
SAFETY SEAL UNDER CAP IS BROKEN OR MISSING

*This product is not manufactured or distributed by
Avrio Health L.P., owner of the registered trademark
Senokot®. 50844 REV1020C29812

100% QC
SATISFACTION
GUARANTEED

Distributed by C.D.M.A., Inc.©
43157 W 9 Mile Rd
Novi, MI 48375
www.qualitychoice.com
Questions: 800-935-2362

Quality Choice 44-298